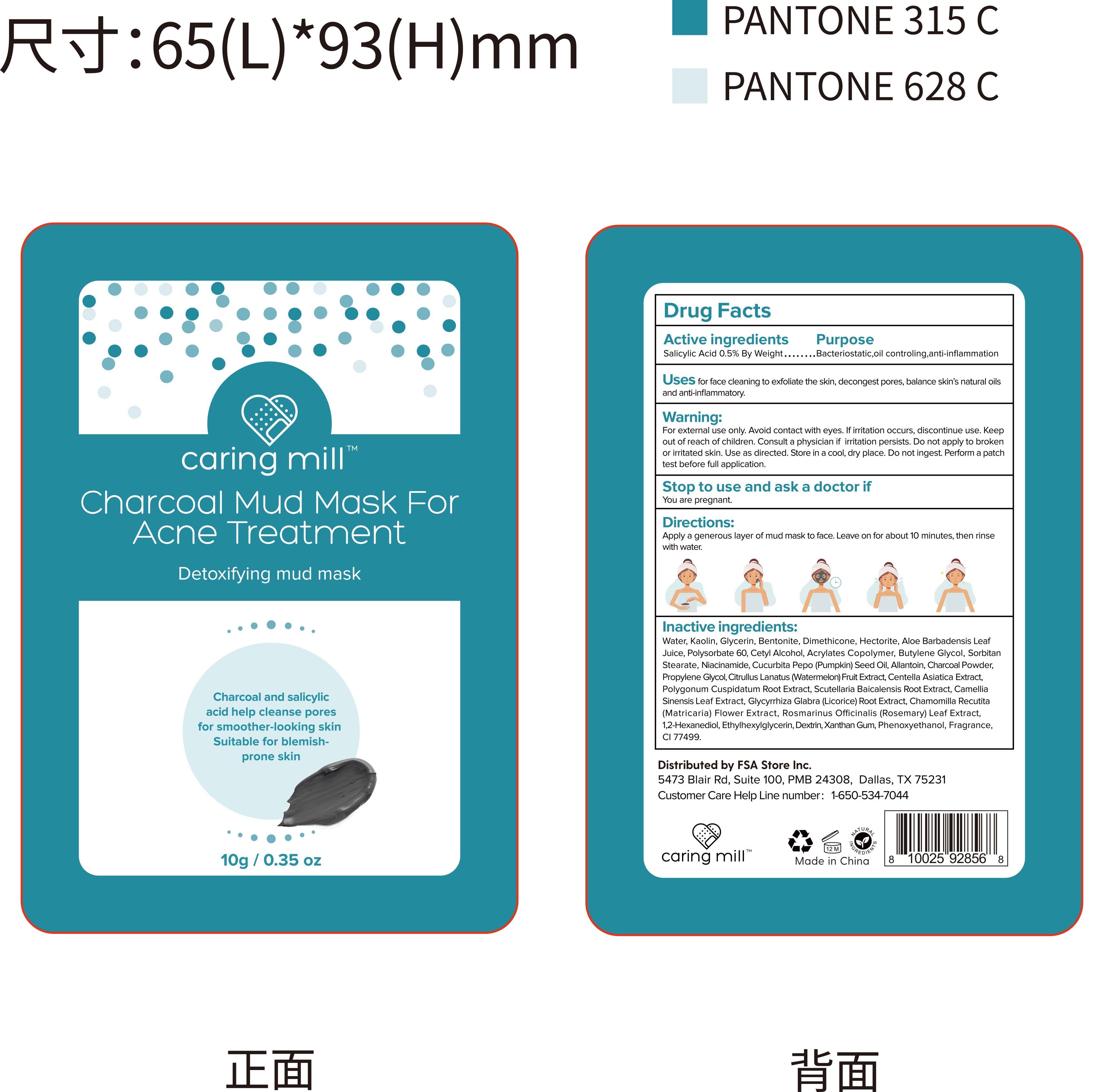 DRUG LABEL: Charcoal Mud Mask For Acne Treatment
NDC: 85783-001 | Form: PASTE
Manufacturer: GUANGZHOU MAGNOLIA BIO TECHNOLOGY CO.,LIMITED
Category: otc | Type: HUMAN OTC DRUG LABEL
Date: 20250630

ACTIVE INGREDIENTS: SALICYLIC ACID 0.05 g/10 g
INACTIVE INGREDIENTS: SCUTELLARIA BAICALENSIS ROOT; WATER; GLYCERIN; CUCURBITA PEPO (PUMPKIN) SEED OIL; XANTHAN GUM; ETHYLHEXYLGLYCERIN; CETYL ALCOHOL; SORBITAN STEARATE; BENTONITE; DIMETHICONE; PROPYLENE GLYCOL; BUTYL ACRYLATE/METHYL METHACRYLATE/METHACRYLIC ACID COPOLYMER (18000 MW); ROSMARINUS OFFICINALIS (ROSEMARY) LEAF POWDER; FRAGRANCE 13576; CHAMOMILE; ALOE BARBADENSIS LEAF JUICE; POLYSORBATE 60; CI 77499; NIACINAMIDE; GLYCYRRHIZA GLABRA (LICORICE) ROOT; HECTORITE; BUTYLENE GLYCOL; ALLANTOIN; POLYGONUM CUSPIDATUM ROOT; PHENOXYETHANOL; CHARCOAL POWDER; CAMELLIA SINENSIS LEAF; DEXTRIN, CORN; KAOLIN; WATERMELON; CENTELLA ASIATICA TRITERPENOIDS; 1,2-HEXANEDIOL

85783-001 Charcoal Mud Mask For Acne Treatment

ACTIVE INGREDIENT

Salicylic Acid 0.5%

PURPOSE

Bacteriostatic,oil controling,anti-inflammation

INDICATIONS AND USAGE

Uses for face cleaning to exfoliate the skin, decongest pores, balance skin's
natural oils and anti-inflammatory.

WARNINGS

For external use only.

Do not applyto broken or irritated skin.

WHEN USING

Avoid contact with eyes.
Do not ingest.

Use as directed. Store in a cool, dry place.

Perform a patch test before ful application.

lf irritation occurs, discontinue use.

You are pregnant.

Keep out of reach of children.

DOSAGE AND ADMINISTRATION

Apply a generous layer of mud mask to face. Leave on for about 10 minutes then rinse with water.

INACTIVE INGREDIENT

Water
Kaolin
Glycerin
Bentonite
Dimethicone
Hectorite
Aloe Barbadensis Leaf Juice
Polysorbate 60
Cetyl Alcohol
Acrylates Copolymer
CI 77499
Butylene Glycol
Sorbitan Stearate
Niacinamide
Phenoxyethanol
Cucurbita Pepo (Pumpkin) Seed Oil
Xanthan Gum
Allantoin
Charcoal Powder
Fragrance
Propylene Glycol
Citrullus Lanatus (Watermelon) Fruit Extract
Centella Asiatica Extract
Polygonum Cuspidatum Root Extract
Scutellaria Baicalensis Root Extract
Camellia Sinensis Leaf Extract
Glycyrrhiza Glabra (Licorice) Root Extract
Chamomilla Recutita (Matricaria) Flower Extract
Rosmarinus Officinalis (Rosemary) Leaf Extract
1,2-Hexanediol
Ethylhexylglycerin
Dextrin